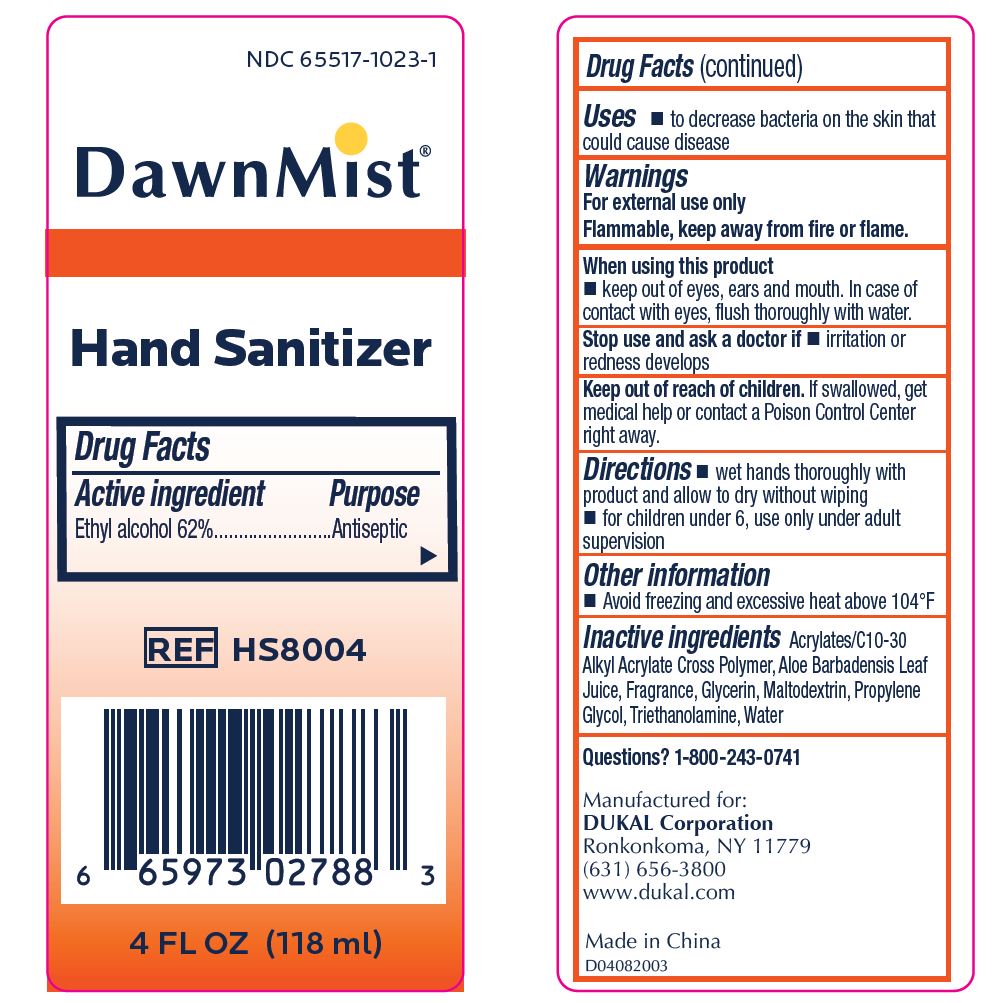 DRUG LABEL: DawnMist Alcohol Hand Sanitizer
NDC: 65517-1023 | Form: GEL
Manufacturer: Dukal LLC
Category: otc | Type: HUMAN OTC DRUG LABEL
Date: 20231013

ACTIVE INGREDIENTS: ALCOHOL 0.62 mL/1 mL
INACTIVE INGREDIENTS: TROLAMINE; WATER; CARBOMER INTERPOLYMER TYPE A (55000 CPS); MALTODEXTRIN; ALOE VERA LEAF; GLYCERIN; PROPYLENE GLYCOL

DawnMist Hand Sanitizer

Active Ingredient

Ethyl Alcohol 62%

Purpose

Antiseptic

Use

To decrease bacteria on the skin that could cause disease

Warning

For external use only

Flammable, keep away from fire or flame.

When using this product

Keep out of eyes, ears and mouth. In case of contact with eyes, flush thoroughly with water.

Stop use and ask a doctor if

irritation or redness develops

Keep out of reach of children

If swallowed, get medical help or contact Poison Control Center right away.

Directions

wet hands thoroughly with products and allow to dry without wiping.

for children under 6, use only under adult supervision

Other Information

Avoid freezing and excessive heat above 104°F

Inactive Ingredients

Acrylates/C10-30Alkyl Acrylate Cross Polymer, Aloe Barbadensis Leaf Juice, Fragrance, Glycerin, Maltodextrin, Propylene Glycol, Triethanolamine, Water

Principle Display Panel

NDC 65517-1023-1

DawnMist ®

Hand Sanitizer

Drug Facts

Active Ingredient Purpose

Ethyl alcohol 62%.........Antiseptic

REF HS8004

4 FL. OZ. (118 ml)